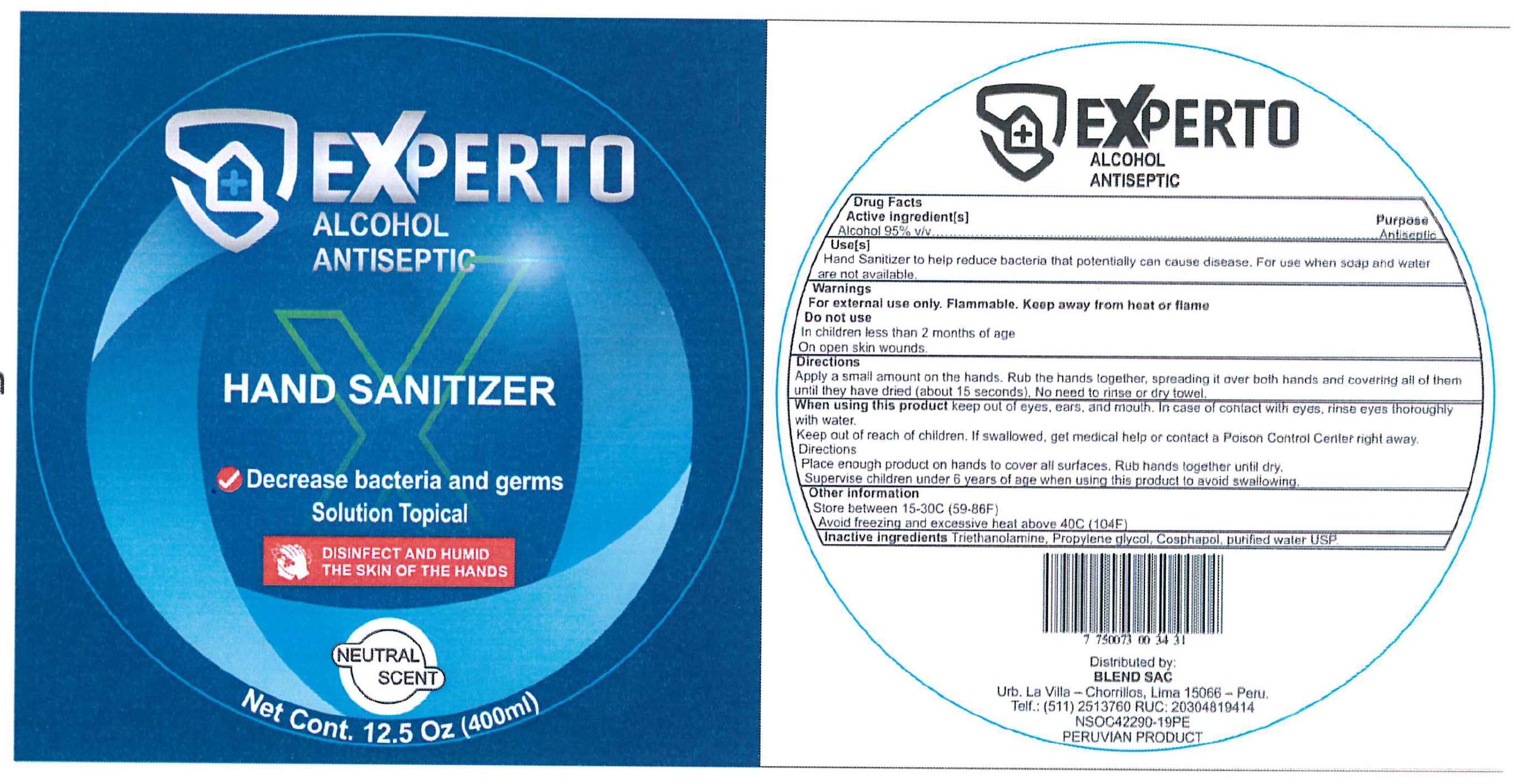 DRUG LABEL: Hand Sanitizer Expert
NDC: 80492-000 | Form: GEL
Manufacturer: BLEND S.A.C.
Category: otc | Type: HUMAN OTC DRUG LABEL
Date: 20201112

ACTIVE INGREDIENTS: ALCOHOL 0.95 mL/1 mL
INACTIVE INGREDIENTS: TROLAMINE; PROPYLENE GLYCOL; CARBOMER HOMOPOLYMER, UNSPECIFIED TYPE; WATER

Hand Sanitizer Expert

Active Ingredient[s]

Alcohol 95% v/v

Purpose

Antiseptic

Use[s]

Hand Sanitizer to help reduce bacteria that potentially can cause disease. For use when soap and water are not available.

Warnings

For external use only. Flammable. Keep away from heat or flame

Do not use

In children less than 2 months of age

On open skin wounds.

When using this product

keep out of eyes, ears, and mouth. In case of contact with eyes, rinse eyes thoroughly with water

Keep out of reach of children.

If swallowed, get medical help or contact a Poison Control Center right away.

Directions

Place enough product on hands to cover all surfaces. Rub hands together until dry.

Supervise children under 6 years of age when using this product to avoid swallowing.

Other Information

Store between 15-30C (59-86F)

Avoid freezing and excessive heat above 40C (104F)

Inactive Ingredients

Triethanolamine, Propylene glycol, cosphapol, purified water USP.